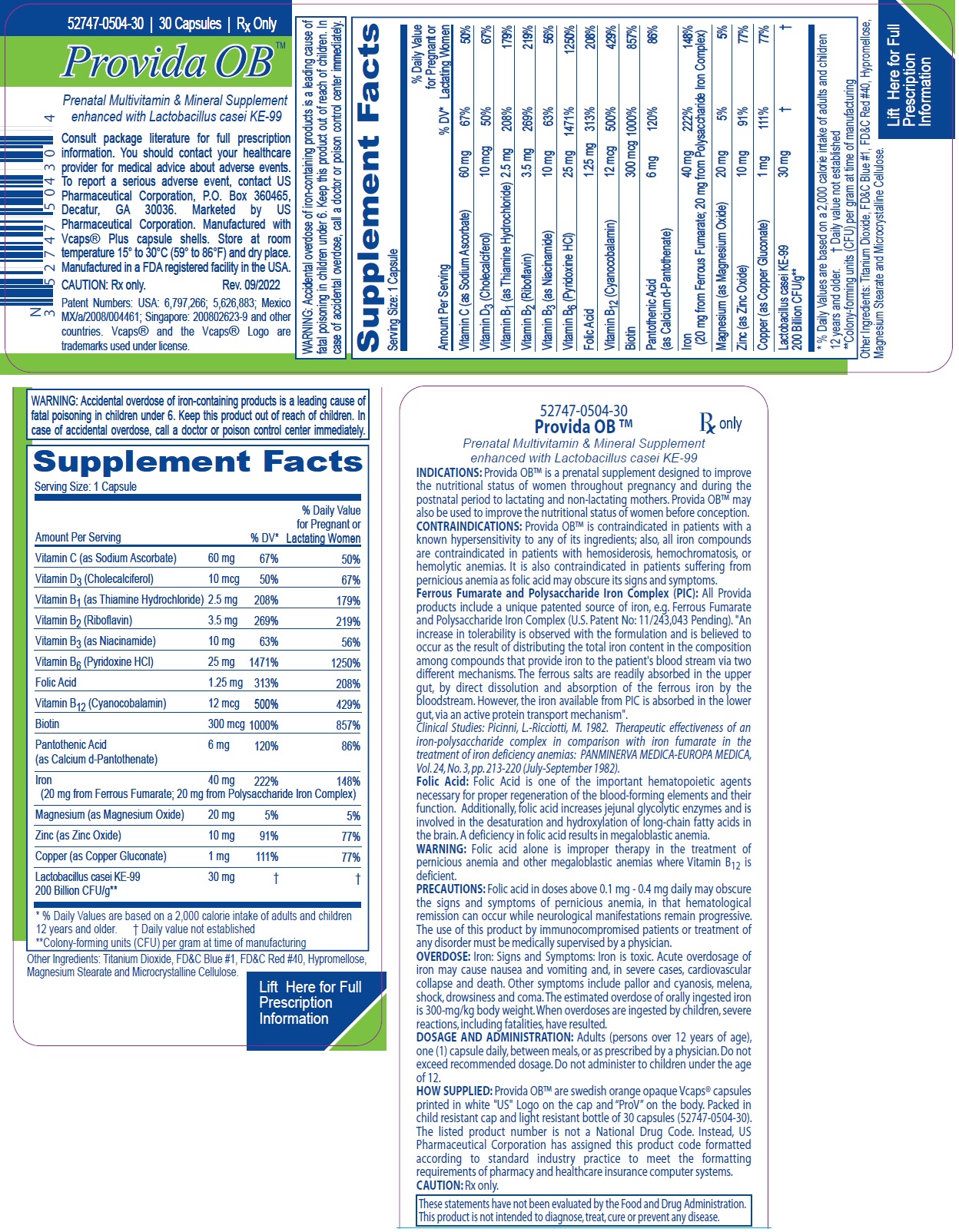 DRUG LABEL: Provida OB
NDC: 52747-504 | Form: CAPSULE
Manufacturer: U.S. Pharmaceutical Corporation
Category: other | Type: Dietary Supplement
Date: 20230614

ACTIVE INGREDIENTS: ASCORBIC ACID 60 mg/1 1; CHOLECALCIFEROL 400 [iU]/1 1; THIAMINE HYDROCHLORIDE 2.5 mg/1 1; RIBOFLAVIN 3.5 mg/1 1; NIACIN 10 mg/1 1; PYRIDOXINE HYDROCHLORIDE 25 mg/1 1; FOLIC ACID 1.25 mg/1 1; CYANOCOBALAMIN 0.012 mg/1 1; BIOTIN 0.3 mg/1 1; CALCIUM PANTOTHENATE 6 mg/1 1; IRON 40 mg/1 1; MAGNESIUM OXIDE 20 mg/1 1; ZINC OXIDE 10 mg/1 1; COPPER GLUCONATE 1 mg/1 1; LACTICASEIBACILLUS CASEI 30 mg/1 1
INACTIVE INGREDIENTS: TITANIUM DIOXIDE; FD&C RED NO. 40; FD&C BLUE NO. 1; HYPROMELLOSE, UNSPECIFIED; MAGNESIUM STEARATE; MICROCRYSTALLINE CELLULOSE

Provida OBTM

STATEMENT OF IDENTITY

Supplement Facts
Serving Size: 1 Capsule
Amount Per Serving |  | % DV* | % Daily Value; for Pregnant or; Lactating Women
Vitamin C (as Sodium Ascorbate) | 60 mg | 67% | 50%
Vitamin D3 (Cholecalciferol) | 10 mcg | 50% | 67%
Vitamin B1 (as Thiamine Hydrochloride) | 2.5 mg | 208% | 179%
Vitamin B2 (Riboflavin) | 3.5 mg | 269% | 219%
Vitamin B3 (as Niacinamide) | 10 mg | 63% | 56%
Vitamin B6 (Pyridoxine HCl) | 25 mg | 1471% | 1250%
Folic Acid | 1.25 mg | 313% | 208%
Vitamin B12 (Cyanocobalamin) | 12 mcg | 500% | 429%
Biotin | 300 mcg | 1000% | 857%
Pantothenic Acid (as Calcium d-Pantothenate) | 6 mg | 120% | 86%
Iron (20 mg from Ferrous Fumarate; 20 mg from Polysaccharide Iron Complex) | 40 mg | 222% | 148%
Magnesium (as Magnesium Oxide) | 20 mg | 5% | 5%
Zinc (as Zinc Oxide) | 10 mg | 91% | 77%
Copper (as Copper Gluconate) | 1 mg | 111% | 77%
Lactobacillus casei KE-99 200 Billion CFU/g** | 30 mg | † | †
* % Daily Values are based on a 2,000 calorie intake of adults and children 12 years and older. † Daily value not established
**Colony-forming units (CFU) per gram at time of manufacturing

Other Ingredients: Titanium Dioxide, FD&C Blue #1, FD&C Red #40, Hypromellose, Magnesium Stearate and Microcrystalline Cellulose.

INDICATIONS: Provida OB™ is a prenatal supplement designed to improve the nutritional status of women throughout pregnancy and during the postnatal period to lactating and non-lactating mothers. Provida OB™ may also be used to improve the nutritional status of women before conception.

CONTRAINDICATIONS: Provida OB™ is contraindicated in patients with a known hypersensitivity to any of its ingredients; also, all iron compounds are contraindicated in patients with hemosiderosis, hemochromatosis, or hemolytic anemias. It is also contraindicated in patients suffering from pernicious anemia as folic acid may obscure its signs and symptoms.

Ferrous Fumarate and Polysaccharide Iron Complex (PIC): All Provida products include a unique patented source of iron, e.g. Ferrous Fumarate and Polysaccharide Iron Complex (U.S. Patent No: 11/243,043 Pending). "An increase in tolerability is observed with the formulation and is believed to occur as the result of distributing the total iron content in the composition among compounds that provide iron to the patient's blood stream via two different mechanisms. The ferrous salts are readily absorbed in the upper gut, by direct dissolution and absorption of the ferrous iron by the bloodstream. However, the iron available from PIC is absorbed in the lower gut, via an active protein transport mechanism".

Clinical Studies: Picinni, L.-Ricciotti, M. 1982. Therapeutic effectiveness of an iron-polysaccharide complex in comparison with iron fumarate in the treatment of iron deficiency anemias: PANMINERVA MEDICA-EUROPA MEDICA, Vol. 24, No. 3, pp. 213-220 (July-September 1982).

Folic Acid: Folic Acid is one of the important hematopoietic agents necessary for proper regeneration of the blood-forming elements and their function. Additionally, folic acid increases jejunal glycolytic enzymes and is involved in the desaturation and hydroxylation of long-chain fatty acids in the brain. A deficiency in folic acid results in megaloblastic anemia.

WARNINGS

WARNING: Accidental overdose of iron-containing products is a leading cause of fatal poisoning in children under 6. Keep this product out of reach of children. In case of accidental overdose, call a doctor or poison control center immediately.

WARNING: Folic acid alone is improper therapy in the treatment of pernicious anemia and other megaloblastic anemias where Vitamin B12 is deficient.

PRECAUTIONS

PRECAUTIONS: Folic acid in doses above 0.1 mg - 0.4 mg daily may obscure the signs and symptoms of pernicious anemia, in that hematological remission can occur while neurological manifestations remain progressive. The use of this product by immunocompromised patients or treatment of any disorder must be medically supervised by a physician.

OVERDOSE: Iron: Signs and Symptoms: Iron is toxic. Acute overdosage of iron may cause nausea and vomiting and, in severe cases, cardiovascular collapse and death. Other symptoms include pallor and cyanosis, melena, shock, drowsiness and coma. The estimated overdose of orally ingested iron is 300-mg/kg body weight. When overdoses are ingested by children, severe reactions, including fatalities, have resulted.

DOSAGE AND ADMINISTRATION: Adults (persons over 12 years of age), one (1) capsule daily, between meals, or as prescribed by a physician. Do not exceed recommended dosage. Do not administer to children under the age of 12.

HOW SUPPLIED: Provida OB™ are swedish orange opaque Vcaps® capsules printed in white "US" Logo on the cap and “ProV” on the body. Packed in child resistant cap and light resistant bottle of 30 capsules (52747-0504-30). The listed product number is not a National Drug Code. Instead, US Pharmaceutical Corporation has assigned this product code formatted according to standard industry practice to meet the formatting requirements of pharmacy and healthcare insurance computer systems.

SAFE HANDLING WARNING

CAUTION: Rx only.

These statements have not been evaluated by the Food and Drug Administration. This product is not intended to diagnose, treat, cure or prevent any disease.

HEALTH CLAIM

Prenatal Multivitamin & Mineral Supplement enhanced with Lactobacillus casei KE-99

Consult package literature for full prescription information. You should contact your healthcare provider for medical advice about adverse events. To report a serious adverse event, contact US Pharmaceutical Corporation, P.O. Box 360465, Decatur, GA 30036. Marketed by US Pharmaceutical Corporation. Manufactured with Vcaps® Plus capsule shells. Store at room temperature 15° to 30°C (59° to 86°F) and dry place. Manufactured in a FDA registered facility in the USA.

Rev. 09/2022

Patent Numbers: USA: 6,797,266; 5,626,883; Mexico MX/a/2008/004461; Singapore: 200802623-9 and other countries. Vcaps® and the Vcaps® Logo are trademarks used under license.